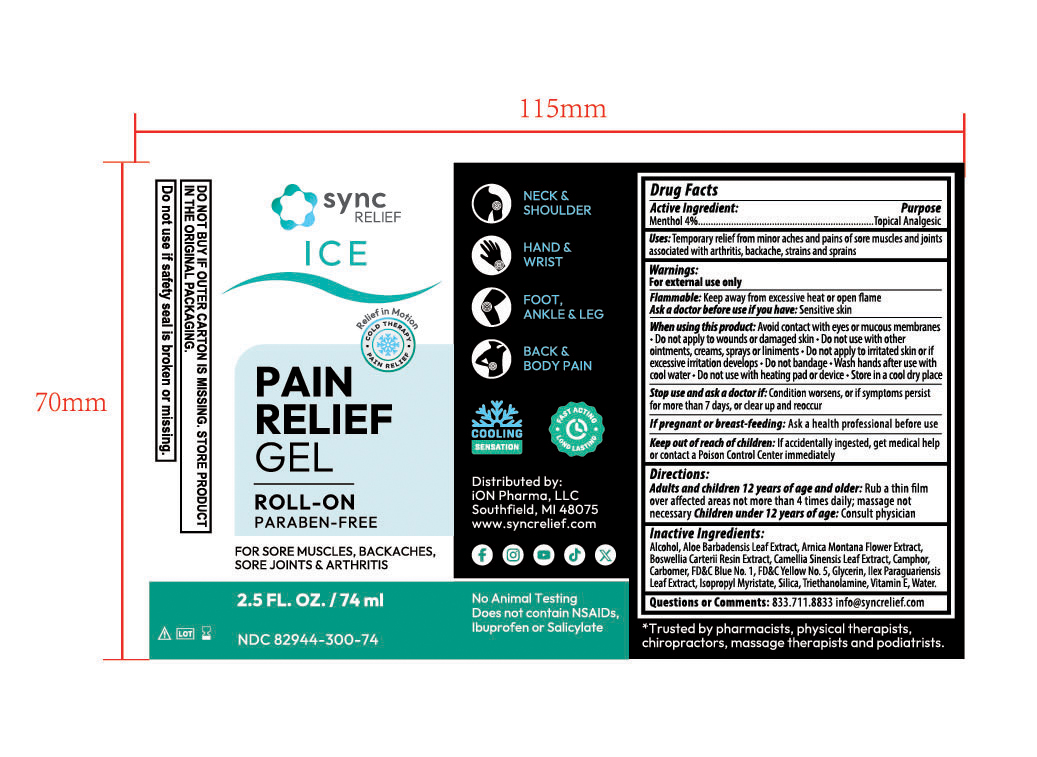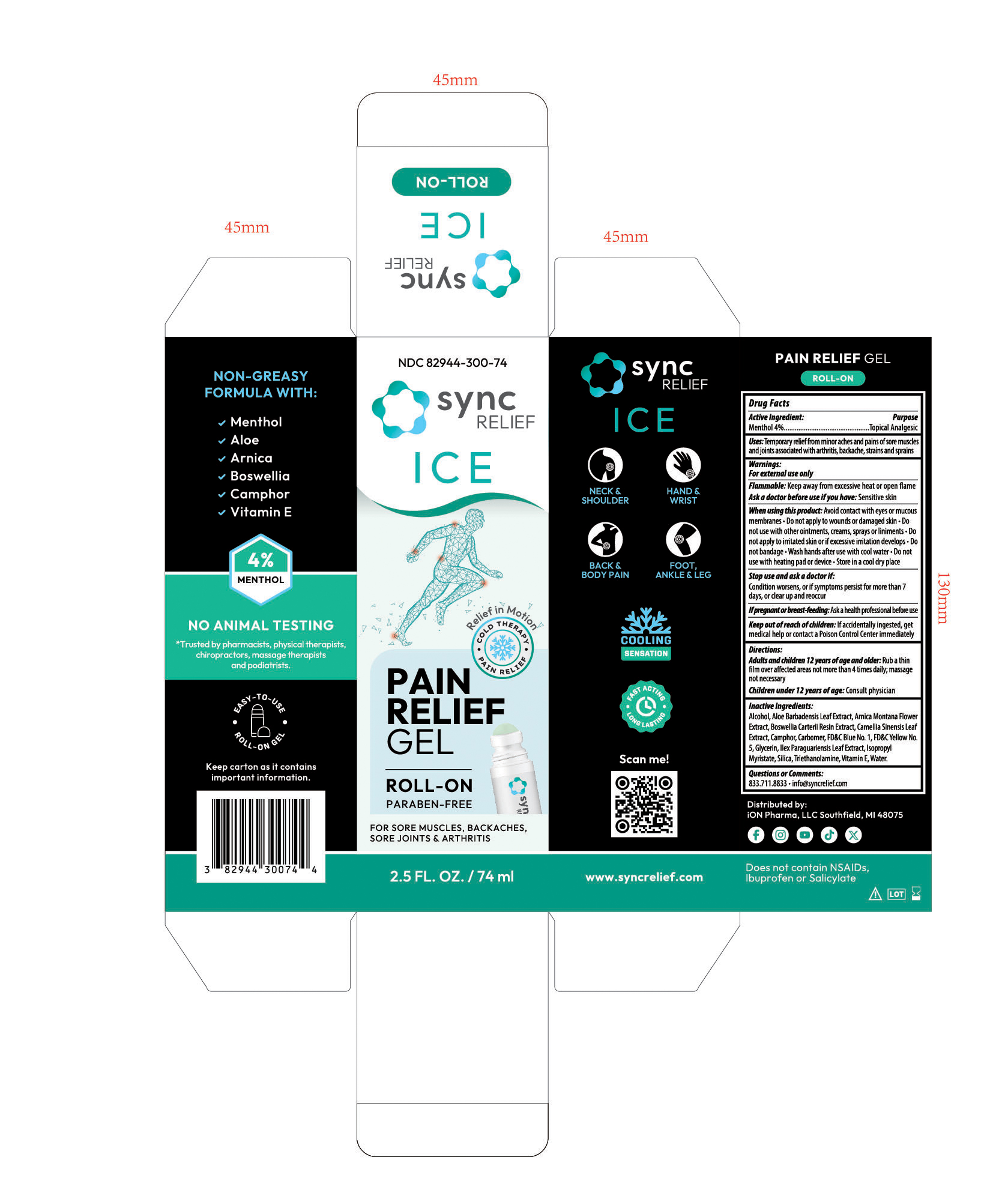 DRUG LABEL: SYNC ICE
NDC: 82944-300 | Form: GEL
Manufacturer: iON Pharma, LLC
Category: otc | Type: HUMAN OTC DRUG LABEL
Date: 20250728

ACTIVE INGREDIENTS: MENTHOL 4 g/1 1
INACTIVE INGREDIENTS: ALCOHOL 95%; ALOE BARBADENSIS LEAF; SILICA; TRIETHANOLAMINE; ALPHA-TOCOPHEROL; WATER; GLYCERIN; FD&C YELLOW NO. 5; FD&C BLUE NO. 1; CAMPHOR (NATURAL); CARBOMER; ARNICA MONTANA FLOWER; CAMELLIA SINENSIS LEAF; ILEX PARAGUARIENSIS LEAF; ISOPROPYL MYRISTATE; BOSWELLIA CARTERII OIL

Sync Relief Ice Roll-on (Menthol 4%)

Drug facts Active ingredient

Drug facts
Active ingredient: purpose

Menthol 4% Topical Analgesic

Uses

Uses: Temporary relief from minor aches and pains of sore muscles and joints associated with arthritis, backache, strains and sprains

Warnings

For external use only

Flammable: Keep away from excessive heat or open flame

Ask a doctor before use if you have: Sensitive skin

When using this product

- Avoid contact with eyes or mucous membranes
- Do not apply to wounds or damaged skin
- Do not use with other ointments, creams, sprays or liniments
- Do no apply to irritated skin or if excessive irritation develops
- Do not bandage
- Wash hands after use with cool water
- Do not use with heating pad or decide
- Store in a cool dry place

Stop use section

Stop use and ask a doctor if:

Condition worsens, or if symptoms persist for more than 7 days, or clear up and reoccur

If pregnant or breast-feeding section

If pregnant or breast-feeding: Ask a healthcare professional before use

Keep out of reach of children: If accidentally ingested, get medical help or contact a Poison Control Center immediately

Directions section

Directions:

Adults and children 12 years of age and older: Rub a thin
thin film over not more than 4 times daily mass; massage
not necessary

Children under 12 years of age: Consult physician

Inactive Ingredients:

Alcohol, Aloe Barbadensis Leaf Extract, Arnica Montana Flower Extract, Boswellia Carterii Resin Extract, Camellia Sinensis Leaf Extract, Camphor, Carbomer, FD&C Blue No. 1, FD&C Yellow No. 5, Glycerin, Ilex Paraguariensis Leaf Extract, Isopropyl Myristate, Silica, Triethanolamine, Vitamin E, Water.

Questions comments section

Questions or Comments:

- 833.711.8833
- info@syncrelief.com

PACKAGE LABEL

NDC 82944-300-74

sync RELIEF ICE

Relief in Motion

COLD THERAPY

PAIN RELIEF

PAIN RELIEF GEL

ROLL-ON

PARABEN-FREE

FOR SORE MUSCLES, BACKACHES, SORE JOINTS & ARTHRITIS

2.5 FL. OZ. / 74 ml

www.syncrelief.com

Does not contain NSAIDs, Ibuprofen, Salicylate